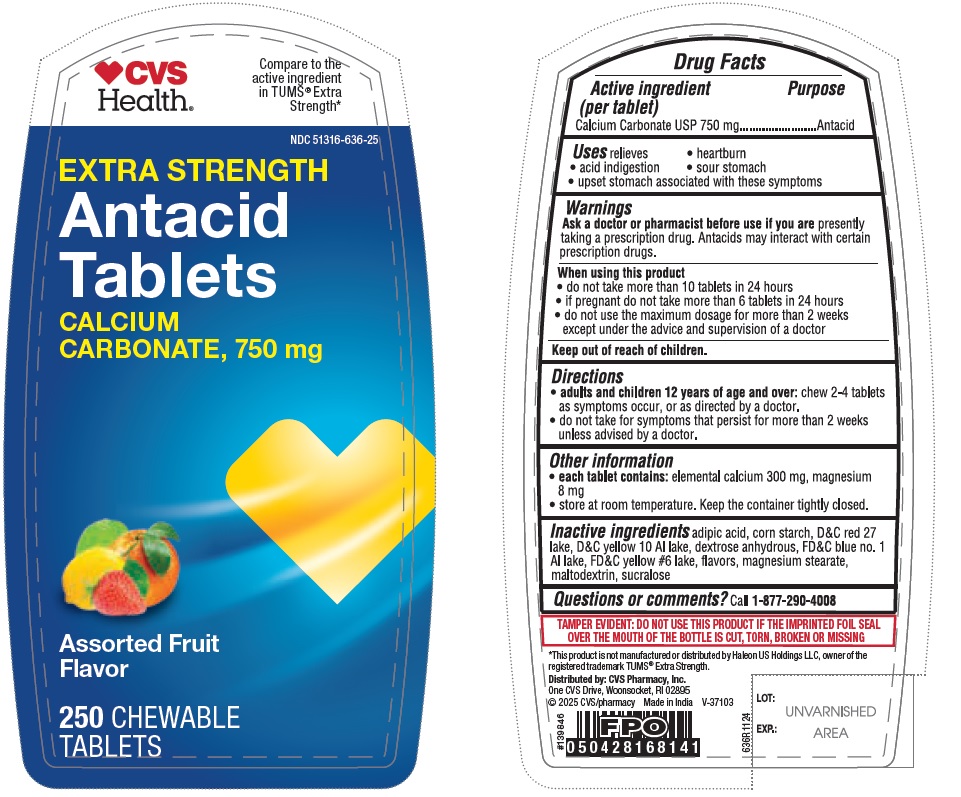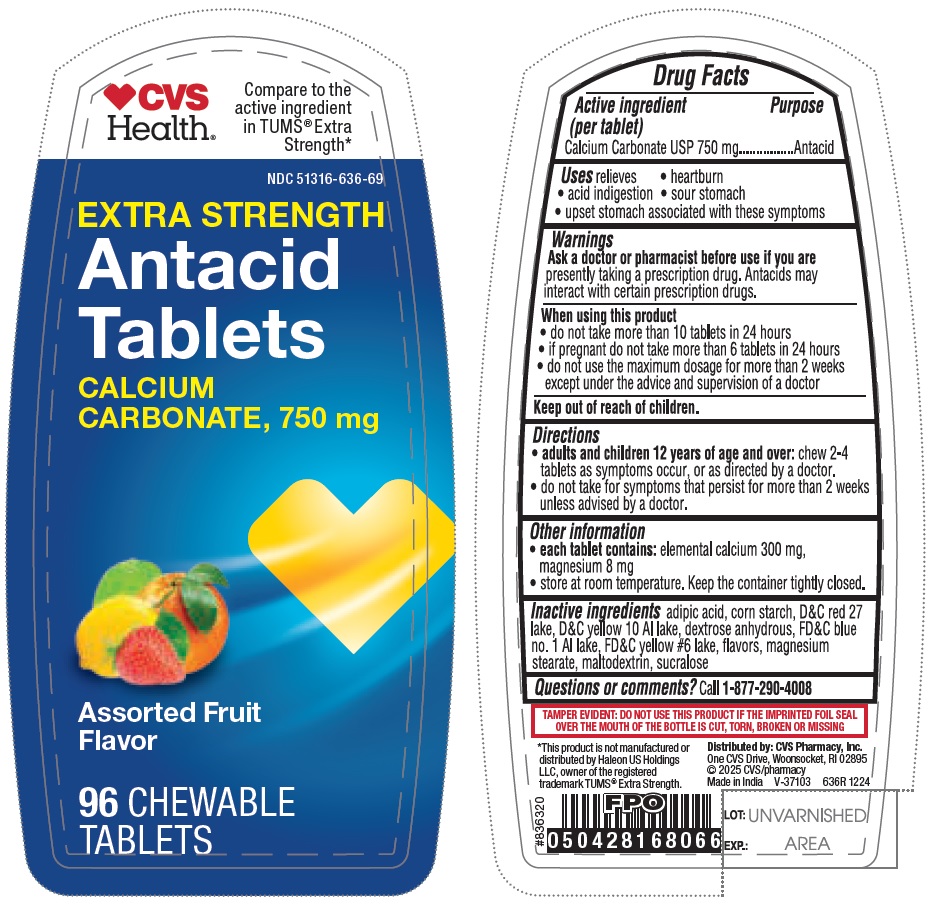 DRUG LABEL: Extra Strength Antacid Calcium Carbonate, 750mg
NDC: 51316-636 | Form: TABLET, CHEWABLE
Manufacturer: CVS HEALTH CORP
Category: otc | Type: HUMAN OTC DRUG LABEL
Date: 20250315

ACTIVE INGREDIENTS: CALCIUM CARBONATE 750 mg/1 1
INACTIVE INGREDIENTS: ANHYDROUS DEXTROSE; MALTODEXTRIN; FD&C YELLOW NO. 6 ALUMINUM LAKE; D&C RED NO. 27 ALUMINUM LAKE; D&C YELLOW NO. 10 ALUMINUM LAKE; FD&C BLUE NO. 1 ALUMINUM LAKE; MAGNESIUM STEARATE; STARCH, CORN; ADIPIC ACID; SUCRALOSE

636R CVS Calcium Carbonate 750 mg chewable tablets - Assorted fruit

Active ingredient (per tablet)

Calcium Carbonate USP 750 mg

Purpose

Antacid

INDICATIONS AND USAGE

Uses relieves

- heartburn
- acid indigestion
- sour stomach
- upset stomach associated with these symptoms

Warnings

Ask a doctor or pharmacist before use if you are presently taking a prescription drug. Antacids may interact with certain prescription drugs.

When using this product

- do not take more than 10 tablets in 24 hours
- if pregnant do not take more than 6 tablets in 24 hours
- do not use the maximum dosage for more than 2 weeks except under the advice and supervision of a doctor

Keep out of reach of children.

Directions

- adults and children 12 years of age and over: chew 2-4 tablets as symptoms occur, or as directed by a doctor.
- do not take for symptoms that persist for more than 2 weeks unless advised by a doctor.

Other information

- each tablet contains: elemental calcium 300 mg, magnesium 8 mg
- store at room temperature. Keep the container tightly closed.

INACTIVE INGREDIENT

Inactive ingredients adipic acid, corn starch, D&C red 27 lake, D&C yellow 10 Al lake, dextrose anhydrous, FD&C blue no. 1 Al lake, FD&C yellow #6 lake, flavors, magnesium stearate, maltodextrin, sucralose

Questions or comments?

Call 1-877-290-4008